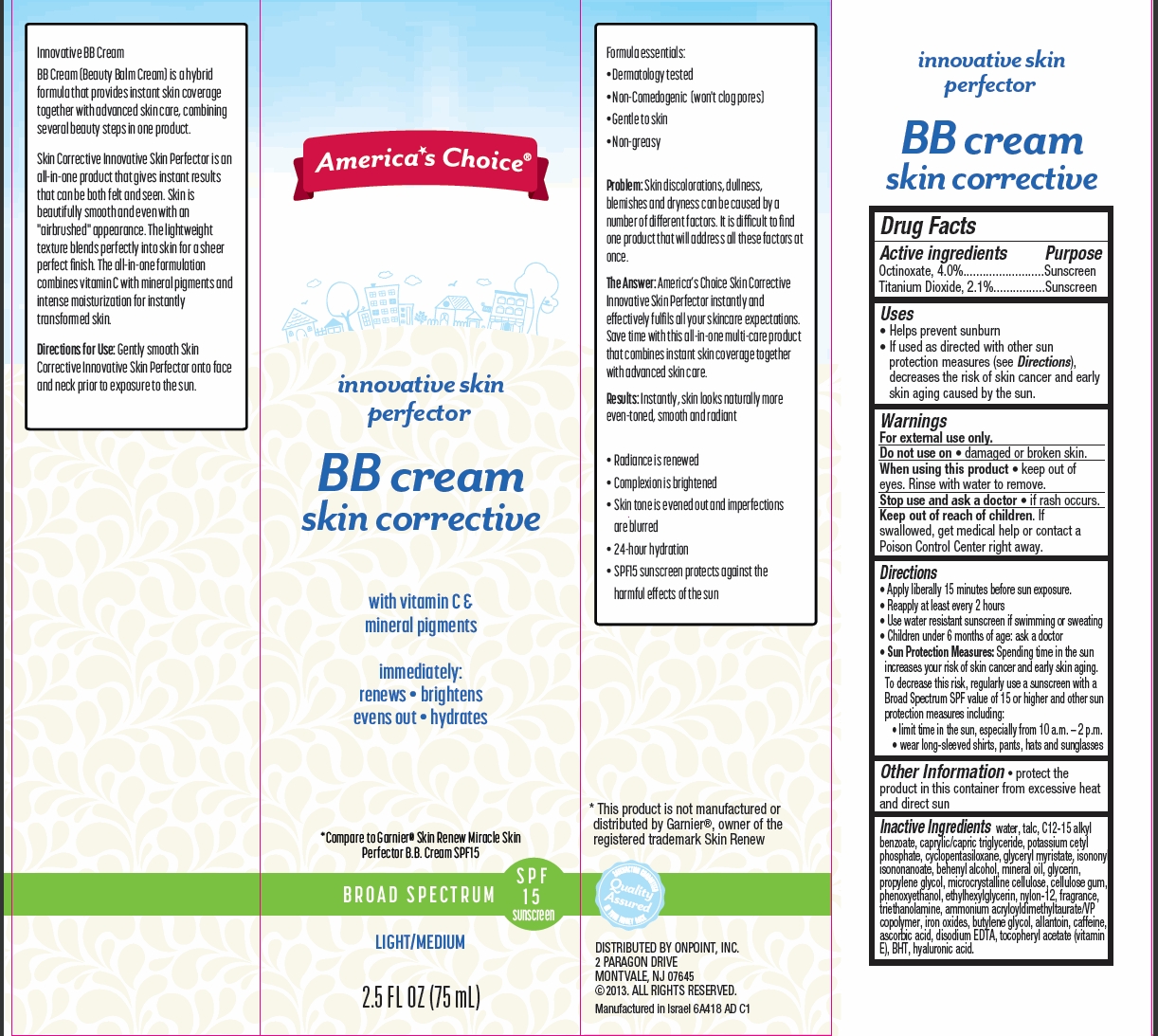 DRUG LABEL: Innovative Skin Perfector BB Broad Spectrum SPF15 Sunscreen (Light/Medium)
NDC: 42421-641 | Form: CREAM
Manufacturer: Emilia Personal Care Inc.
Category: otc | Type: HUMAN OTC DRUG LABEL
Date: 20140915

ACTIVE INGREDIENTS: OCTINOXATE 4 g/100 g; TITANIUM DIOXIDE 2.1 g/100 g
INACTIVE INGREDIENTS: WATER; TALC; ALKYL (C12-15) BENZOATE; MEDIUM-CHAIN TRIGLYCERIDES; POTASSIUM CETYL PHOSPHATE; CYCLOMETHICONE 5; GLYCERYL MYRISTATE; ISONONYL ISONONANOATE; DOCOSANOL; MINERAL OIL; GLYCERIN; PROPYLENE GLYCOL; CELLULOSE, MICROCRYSTALLINE; CARBOXYMETHYLCELLULOSE SODIUM; PHENOXYETHANOL; ETHYLHEXYLGLYCERIN; NYLON-12; TROLAMINE; AMMONIUM ACRYLOYLDIMETHYLTAURATE/VP COPOLYMER; FERROUS OXIDE; BUTYLENE GLYCOL; ALLANTOIN; CAFFEINE; ASCORBIC ACID; EDETATE DISODIUM; .ALPHA.-TOCOPHEROL ACETATE; BUTYLATED HYDROXYTOLUENE; HYALURONIC ACID

America's Choice® innovative skin perfector BB cream skin corrective

Active ingredient

Octinoxate 4.0%
Titanium Dioxide 2.1%

Purpose

Sunscreen

Uses

- Helps prevent sunburn
- If used as directed with other sun protection measures (see Directions), decreases the risk of skin cancer and early skin aging caused by the sun.

Warnings

For external use only.

Do not use on

- damaged or broken skin.

When using this product

- keep out of eyes. Rinse with water to remove.

Stop use and ask a doctor

- if rash occurs.

Keep Out of Reach of Children

If swallowed, get medical help or contact a Poison Control Center right away.

Directions

- Apply liberally 15 minutes before sun exposure.
- Reapply at least every 2 hours
- Use water-resistant sunscreen if swimming or sweating
- Children under 6 months: ask a doctor
- Sun Protection Measures: Spending time in the sun increases your risk of skin cancer and early skin aging. To decrease this risk, regularly use a sunscreen with a Broad Spectrum SPF value of 15 or higher and other sun protection measures including:
  1. limit time in the sun, especially from 10 a.m. - 2 p.m.
  2. wear long-sleeved shirts, pants, hats and sunglasses

Other Information

- protect the product in this container from excessive heat and direct sun

Inactive Ingredients

water, talc, C12-15 alkyl benzoate, caprylic/capric triglyceride, potassium cetyl phosphate, cyclopentasiloxane, glyceryl myristate, isononyl isononanoate, behenyl alcohol, mineral oil, glycerin, propylene glycol, microcrystalline cellulose, cellulose gum, phenoxyethanol, ethylhexylglycerin, nylon-12, fragrance, triethanolamine, ammonium acroloyldimethyltaurate/VP copolymer, iron oxides, butylene glycol, allantoin, caffeine, ascorbic acid, disodium EDTA, tocopheryl acetate (vitamin E), BHT, hyaluronic acid.

Package/Label Principal Display Panel

America's Choice®

innovative skin
perfector

BB cream
skin corrective

with vitamin C &
mineral pigments
immediately:

renews · brightens
  evens out · hydrates

*Compare to Garnier® Skin Renew Miracle Skin
Perfector B.B. Cream SPF15

BROAD SPECTRUM SPF 15 sunscreen

LIGHT/MEDIUM

2.5 FL OZ (75 mL)

*This product is not manufactured or distributed by Garnier®, owner of the registered trademark Skin Renew

DISTRIBUTED BY ONPOINT, INC.
2 PARAGON DRIVE
MONTVALE, NJ 07645
©2013. ALL RIGHTS RESERVED.
Manufactured in Israel 6A418 AD C1

Carton Label